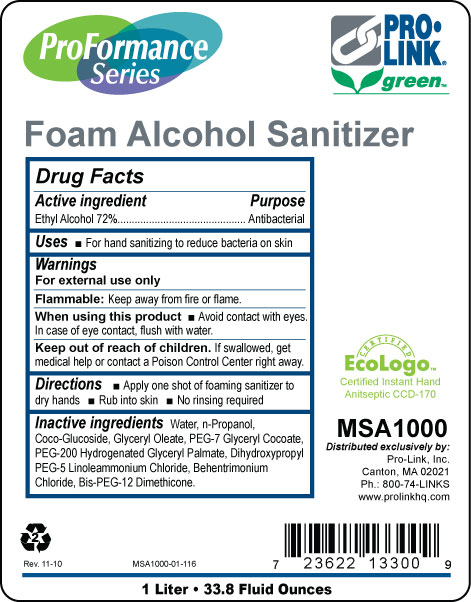 DRUG LABEL: ProFormance Series Foam Alcohol Hand Sanitizer
NDC: 66908-107 | Form: LIQUID
Manufacturer: Pro-Link, Inc.
Category: otc | Type: HUMAN OTC DRUG LABEL
Date: 20110117

ACTIVE INGREDIENTS: ALCOHOL 72 mL/100 mL
INACTIVE INGREDIENTS: WATER; DIHYDROXYPROPYL PEG-5 LINOLEAMMONIUM CHLORIDE; PROPYL ALCOHOL; BEHENTRIMONIUM CHLORIDE

Drug Facts

Active ingredient

Ethyl Alcohol 72%

Purpose

Antibacterial

Uses

For hand sanitizing to reduce bacteria on skin

Warnings

For external use only

Flammable: Keep away from fire or flame.

When using this product avoid contact with eyes.

In case of eye contact, flush with water.

Keep out of reach of children.

If swallowed, get medical help or contact a Poison Control Center right away.

Directions

Apply one shot of foaming sanitizer to dry hands

Rub into skin

No rinsing required

Inactive ingredients

Water, n-Propanol, Bis-PEG-12 Dimethicone, Behentrimonium Chloride, PEG-200 Hydrogenated Glyceryl Palmate, PEG-7 Glyceryl Cocoate, Coco-Glucoside, Glyceryl Oleate, Dihydroxypropyl PEG-5 Linoleammonim Chloride

PACKAGE LABEL

ProFormance Series

Foam Alcohol Sanitizer

Pro-Link Green

Certified EcoLogo

Certified Instant Hand Antiseptic CCD-170

MSA1000

Distributed exclusively by:

Pro-Link, Inc.

1 Liter

33.8 Fluid Ounces